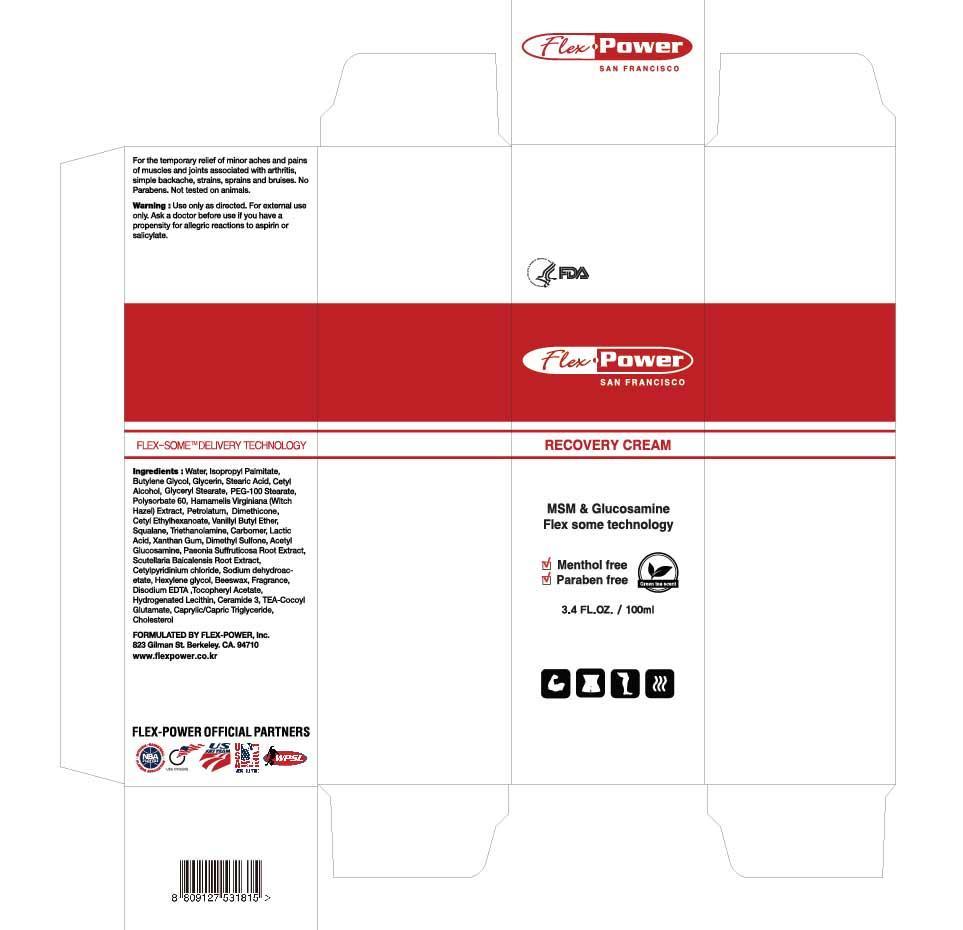 DRUG LABEL: Flex Power Cream
NDC: 69093-1001 | Form: CREAM
Manufacturer: FLEX-POWER KOREA INC
Category: otc | Type: HUMAN OTC DRUG LABEL
Date: 20140704

ACTIVE INGREDIENTS: GLYCERIN 4 g/100 mL
INACTIVE INGREDIENTS: DIMETHICONE; BUTYLENE GLYCOL; GLYCERYL MONOSTEARATE; CETYL ETHYLHEXANOATE; XANTHAN GUM

Drug Facts

ACTIVE INGREDIENT

glycerin

INACTIVE INGREDIENT

water, isopropyl palmitate, butylene glycol, stearic acid, glyceryl stearate, cetyl alcohol, polysorbate 61, witch hazel ext, butylene glycol, pentylene glycol, petrolatum, peg-101 stearate, dimethicone, cetyl ethylhexanoate, vanillyl butyl ether, squalane, triethanolamine, carbomer, lactic acid, xanthan gum, dimethyl sulfone, acetyl glucosamine, paeonia suffruticosa root ext, scutellaria baicalensis root ext, cetyl pyridinium chloride, sodium dehydroacetate, hexylene glycol, beeswax, fragrance, disodium edta, tocopheryl acetate, hydrogenated lecithin, ceramide 4, tea-cocoyl glutamate, caprylic/capric triglyceride, cholesterol

PURPOSE

endless effort to improve performance and passion for healthy lifestyle

keep out of reach of the children

INDICATIONS AND USAGE

massage on body for warming sensation
use apply gradually to build comfort level for warming sensation

WARNINGS

use only as directed
avoid contact with eyes, face, wounds, damaged skin or sensitive areas. if contact occurs, flush with water for 15 minutes

DOSAGE AND ADMINISTRATION

for external use only